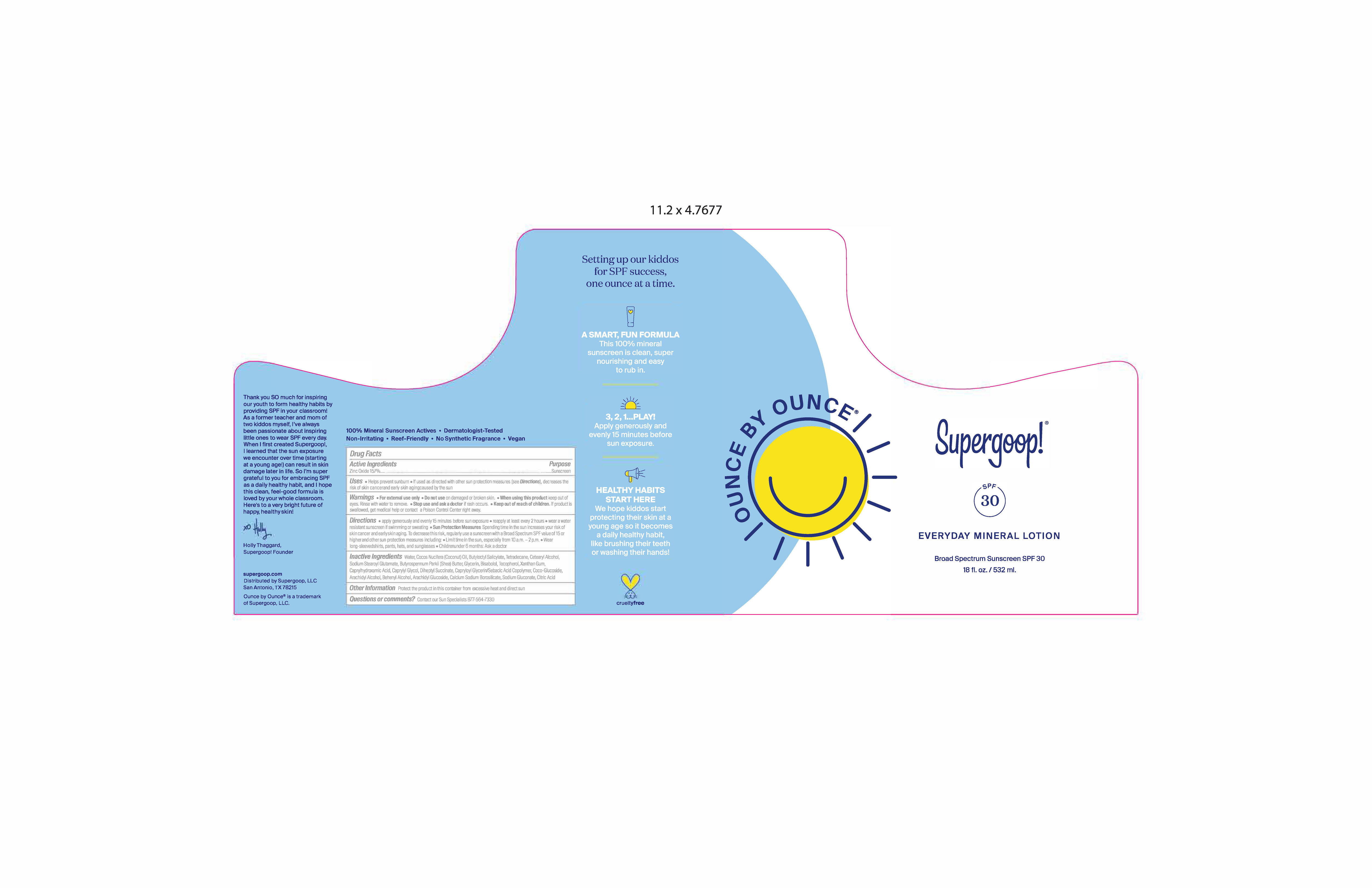 DRUG LABEL: Ounce by Ounce Broad Spectrum Sunscreen SPF 30
NDC: 75936-158 | Form: LOTION
Manufacturer: Supergoop, LLC
Category: otc | Type: HUMAN OTC DRUG LABEL
Date: 20221027

ACTIVE INGREDIENTS: ZINC OXIDE 15.7 g/100 mL
INACTIVE INGREDIENTS: WATER; XANTHAN GUM; BUTYLOCTYL SALICYLATE; SHEA BUTTER; CAPRYLHYDROXAMIC ACID; CITRIC ACID MONOHYDRATE; COCO GLUCOSIDE; TETRADECANE; DIHEPTYL SUCCINATE; DOCOSANOL; COCONUT OIL; ARACHIDYL GLUCOSIDE; TOCOPHEROL; LEVOMENOL; SODIUM STEAROYL GLUTAMATE; CAPRYLOYL GLYCERIN/SEBACIC ACID COPOLYMER (2000 MPA.S); GLYCERIN; SODIUM GLUCONATE; ARACHIDYL ALCOHOL; CAPRYLYL GLYCOL; CETOSTEARYL ALCOHOL

Ounce by Ounce Lotion Broad Spectrum Sunscreen SPF 30

Active Ingredients Purpose

Zinc Oxide 15.7% Sunscreen

Uses

- Helps prevent sunburn
- If used as directed with other sun protection measures (see Directions), decreases the risk of skin cancer and early skin aging caused by the sun

- Keep out of reach of children.
- If product is swallowed, get medical help or contact a Poison Control Center right away.

Stop use and ask a doctor if rash occurs

Warnings For external use only

- Do not use on damaged or broken skin
- When using this product keep out of eyes
- Rinse with water to remove

Directions

- Apply generously and evenly 15 minutes before sun exposure
- reapply at least every 2 hours
- wear a water resistant sunscreen if swimming or sweating.
- Sun Protection Measures Spending time in the sun increases your risk of skin cancer and early skin aging. To decrease this risk, regularly use a sunscreen with a Broad Spectrum value of 15 or higher and other sun protection measures including
- Limit time in the sun, especially from 10 a.m. - 2 p.m.
- Wear Long-sleeved shirts, pants, hats, and sunglasses
- Children under 6 months: Ask a doctor

Inactive Ingredient Arachidyl Alcohol, Arachidyl Glucoside, Behenyl Alcohol, Bisabolol, Butyloctyl Salicylate, Butyrospermum Parkii (Shea) Butter, Calcium Sodium Borosilicate, Caprylhydroxamic Acid, Capryloyl Glycerin/Sebacic Acid Copolymer, Caprylyl Glycol, Cetearyl Alcohol, Citric Acid, Coco-Glucoside, Cocos Nucifera (Coconut) Oil, Diheptyl Succinate, Glycerin, Sodium Gluconate, Sodium Stearoyl Glutamate, Tetradecane, Tocopherol, Water, Xanthan Gum

Other Information Protect the product in this container from excessive heat and direct sun

PACKAGE LABEL

Ounce by Ounce

Supergoop

SPF 30

Everyday Mineral Lotion

Broad Spectrum Sunscreen SPF 30

18 fl. oz. / 532 ml.